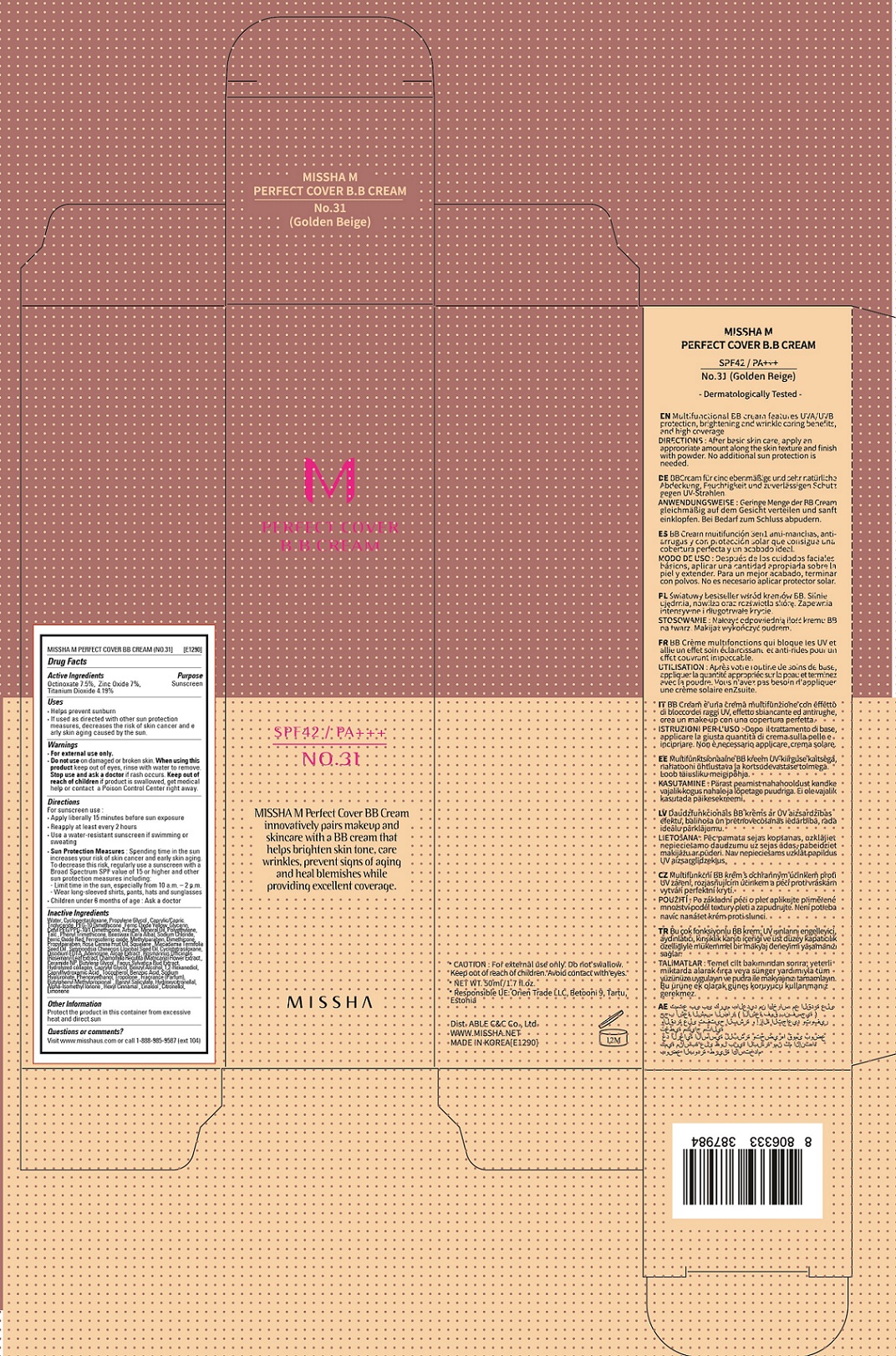 DRUG LABEL: MISSHA M Perfect Cover BB No 31
NDC: 13733-181 | Form: CREAM
Manufacturer: Able C&C Co., Ltd.
Category: otc | Type: HUMAN OTC DRUG LABEL
Date: 20241205

ACTIVE INGREDIENTS: ZINC OXIDE 0.07 g/1 g; TITANIUM DIOXIDE 0.0419 g/1 g; OCTINOXATE 0.075 g/1 g
INACTIVE INGREDIENTS: MACADAMIA OIL; EDETATE DISODIUM ANHYDROUS; CERAMIDE 6 II; FAGUS SYLVATICA FLOWER BUD; BUTYLENE GLYCOL; PROPYLENE GLYCOL; PEG-10 DIMETHICONE (600 CST); TOCOPHEROL; BENZOIC ACID; HYALURONATE SODIUM; TROPOLONE; 1,2-HEXANEDIOL; WATER; CYCLOMETHICONE; PHENOXYETHANOL; TALC; SODIUM CHLORIDE; FERRIC OXIDE YELLOW; METHYLPARABEN; FERRIC OXIDE RED; SQUALANE; ARBUTIN; MEDIUM-CHAIN TRIGLYCERIDES; GLYCERIN; ABRONIA VILLOSA LEAF; YELLOW WAX; DIMETHICONE; PROPYLPARABEN; LAMINARIA HYPERBOREA; ROSEMARY; BENZYL ALCOHOL; CYCLOMETHICONE 4; JOJOBA OIL; FERROSOFERRIC OXIDE; ADENOSINE; CHAMOMILE FLOWER OIL; MINERAL OIL; TRIS(TRIMETHYLSILOXY)PHENYLSILANE; CAPRYLYL GLYCOL; CAPRYLHYDROXAMIC ACID; HIGH DENSITY POLYETHYLENE

MISSHA M Perfect Cover BB No 31

Active Ingredient

Active Ingredients: Octinoxate 7.5%, Zinc Oxide 7%, Titanium Dioxide 4.19%

Purpose

Sunscreen

Uses

- helps prevent sunburn
- if used as directed with other sun protection measures (see Directions), decreases the risk of skin cancer and early skin aging caused by the sun

Directions

- apply liberally 15 minutes before sun exposure
- reapply at least every 2 hours
- use a water-resistant sunscreen if swimming or sweating

Sun protection Measures.Spending time in the sun increases your risk of skin cancer and early skin aging. To decrease this risk, regulary use a sunscreen with SPF value of 15 or higher and other sun protection measures including:

- limit time in the sun, especially from 10 a.m. - 2 p.m.
- wear long-sleeved shirts, pants, hats and sunglasses

Other Information

protect the product in this container from excessive heat and direct sun.

Questions or comments?

visit www.misshaus.com or call 1-888-985-9887(Ext 104)

INACTIVE INGREDIENT

Water, Cyclopentasiloxane, Propylene Glycol, Caprylic/Capric Triglyceride, PEG-10 Dimethicone, Glycerin, Cetyl PEG/PPG-10/1 Dimethicone, Arbutin, Mineral Oil, Polyethylene, Talc, Phenyl Trimethicone, Beeswax (Cera Alba), Sodium Chloride, Ferric Oxide Yellow, Methylparaben, Dimethicone, Ferric Oxide Red, Propylparaben, Rosa Canina Fruit Oil, Squalane, Macadamia Ternifolia Seed Oil, Simmondsia Chinensis (Jojoba) Seed Oil, Cyclotetrasiloxane, Ferrosoferric oxide, Disodium EDTA, Adenosine, Algae Extract, Rosmarinus Officinalis (Rosemary) Leaf Extract, Chamomilla Recutita (Matricaria) Flower Extract, Ceramide NP, Butylene Glycol, Fagus Sylvatica Bud Extract, Hydrolyzed collagen, Caprylyl Glycol, Benzyl Alcohol, 1,2-Hexanediol, Caprylhydroxamic Acid, Tocopherol, Benzoic Acid, Sodium Hyaluronate, Phenoxyethanol, Tropolone, Fragrance (Parfum), Butylphenyl Methylpropional, Benzyl Salicylate, Hydroxycitronellal, Alpha-Isomethyl Ionone, Hexyl Cinnamal, Linalool, Citronellol, Limonene

Warnings:
Do not use on damaged or broken skin.
When using this product, keep out of eyes. Rinse with water to Remove.
Stop use and ask a doctor, if rash ocurs.

Keep out of reach of children.